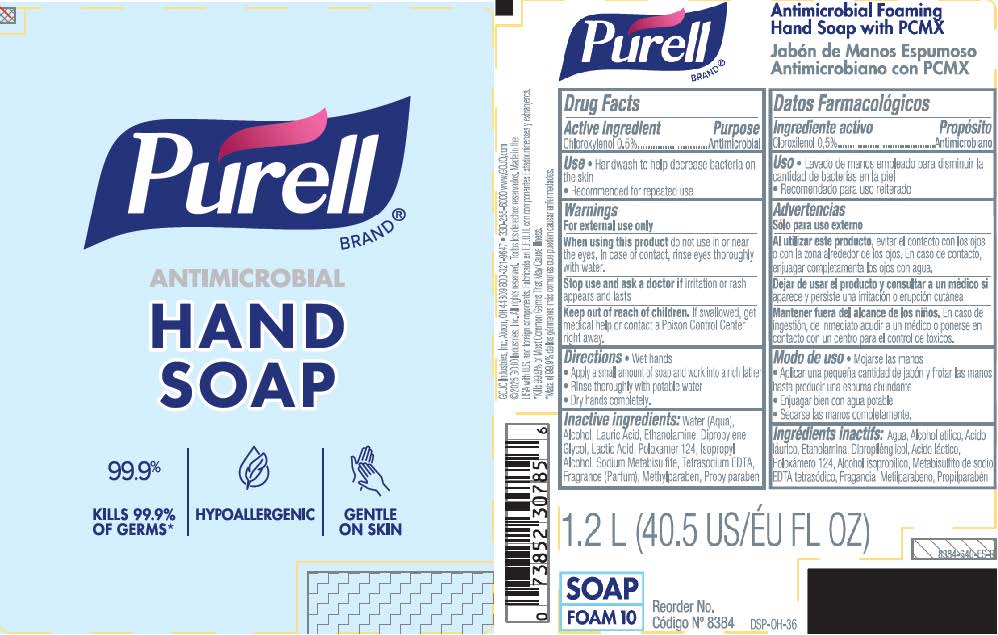 DRUG LABEL: PURELL Antimicrobial Foaming Hand SP with PCMX
NDC: 21749-722 | Form: LIQUID
Manufacturer: GOJO Industries, Inc.
Category: otc | Type: HUMAN OTC DRUG LABEL
Date: 20251124

ACTIVE INGREDIENTS: CHLOROXYLENOL 0.5 mg/100 mL
INACTIVE INGREDIENTS: WATER; ALCOHOL; LAURIC ACID; MONOETHANOLAMINE; DIPROPYLENE GLYCOL; LACTIC ACID; POLOXAMER 124; ISOPROPYL ALCOHOL; SODIUM METABISULFITE; EDETATE SODIUM; METHYLPARABEN; PROPYLPARABEN

PURELL HEALTHY SOAP 0.5% PCMX Antimicrobial Foam

Active Ingredient

Chloroxylenol 0.5%

Purpose

Microbial

Use

• Handwash to help decrease bacteria on the skin.

• Recommended for repeated use.

Warnings

When using this product do not use in or near the eyes. In case of contact, rinse eyes thoroughly with water.

Stop use and ask a doctor if irritation or rash appears and lasts.

Keep out of reach of children. If swallowed, get medical help or contact a Poison Control Center right away.

Directions

• Wet hands

• Apply a small amount of soap and work into a rich lather

• Rinse thoroughly with potable water

• Dry hands completely.

Inactive Ingredients

Water (Aqua), Alcohol, Lauric Acid, Ethanolamine, Dipropylene Glycol, Lactic Acid, Poloxamer 124, Isopropyl Alcohol, Sodium Metabisulfite, Tetrasodium EDTA, Fragrance (Parfum), Methylparaben, Propylparaben